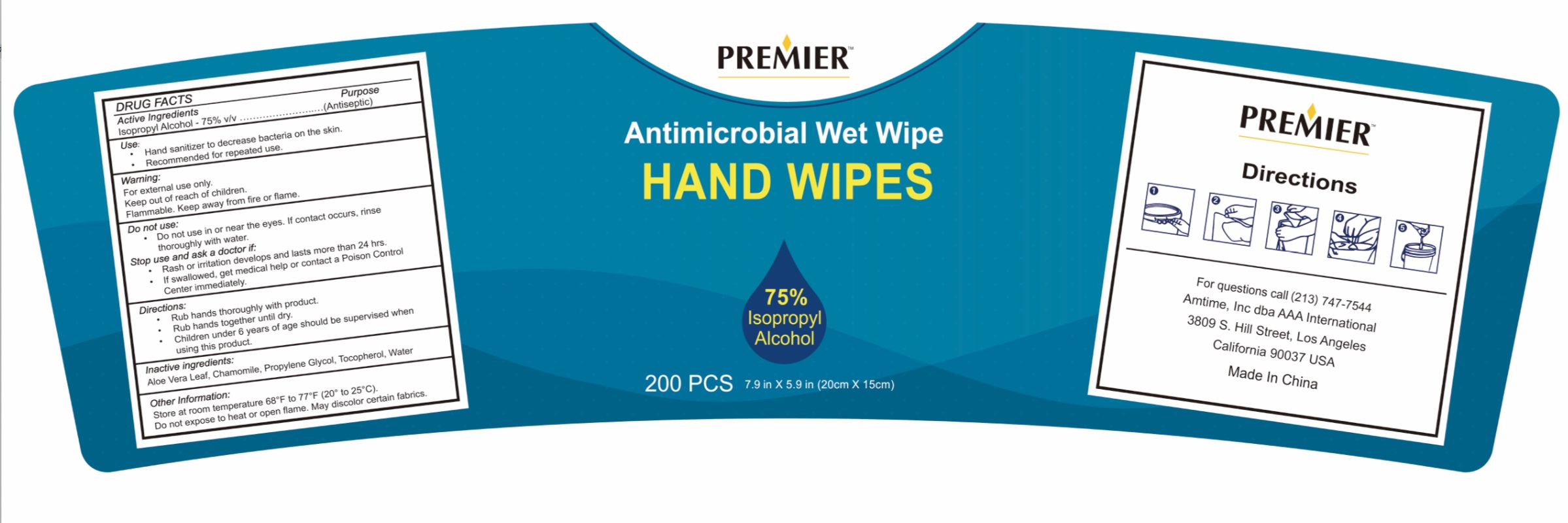 DRUG LABEL: ISOPROPYL ALCOHOL
NDC: 83290-001 | Form: CLOTH
Manufacturer: Amtime, Inc.
Category: otc | Type: HUMAN OTC DRUG LABEL
Date: 20230221

ACTIVE INGREDIENTS: ISOPROPYL ALCOHOL 2.97 g/1 1
INACTIVE INGREDIENTS: CHAMOMILE; PROPYLENE GLYCOL; TOCOPHEROL; WATER; ALOE VERA LEAF

200 WET WIPES 83290-001-1

Active ingredients

ISOPROPYL ALCOHOL - 75% v/v ..............................................(Antiseptic)

USE

Hand sanitizer to decrease bacteria on the skin.

Recommended for repeated use.

INDICATIONS AND USAGE

Clean hands to avoid bacterial infection

Warning

For extenal use only.

Flammable. Keep away from fire or flame.

keep out of reach of children.

Do not use in or near the eyes. lf contact occurs, rinse thoroughly with water.

Stop use and ask a doctor if

Rash or irritation develops and lasts more than 24 hrs.
lf swallowed , get medical help or contact a Poison ControlCenter immediately.

DOSAGE AND ADMINISTRATION

Rub hands thoroughly with product.
Rub hands together until dry.
Children under 6 years of age should be supervised whenusing this product.

Inactive ingredients

ALOE VERA LEAF, CHAMOMILE, PROPYLENE GLYCOL, TOCOPHEROL, WATER

Other Information

Store at room temperature 68°F to 77°F(20° to 25°C).
Do not expose to heat or open flame. May discolor certain fabrics.